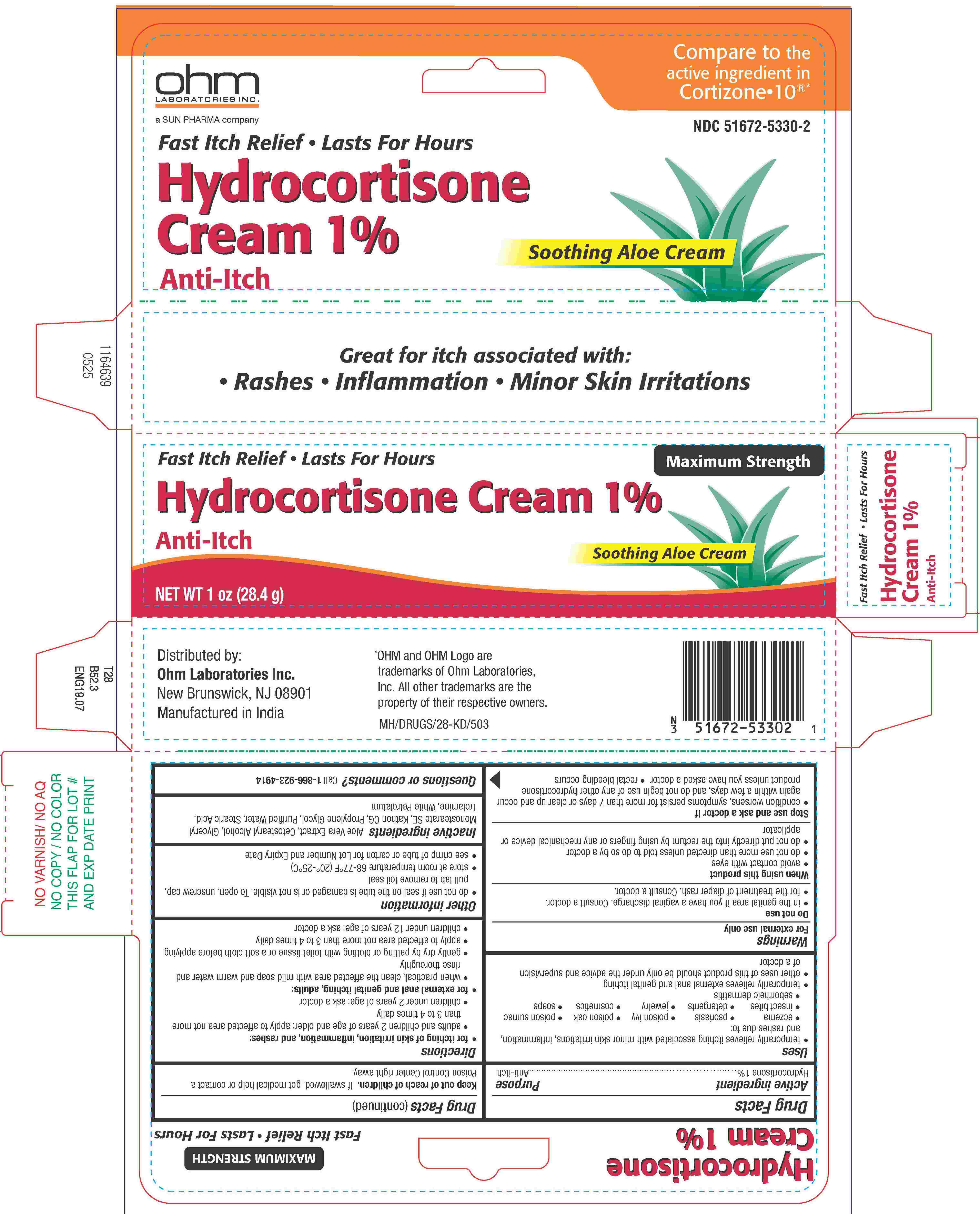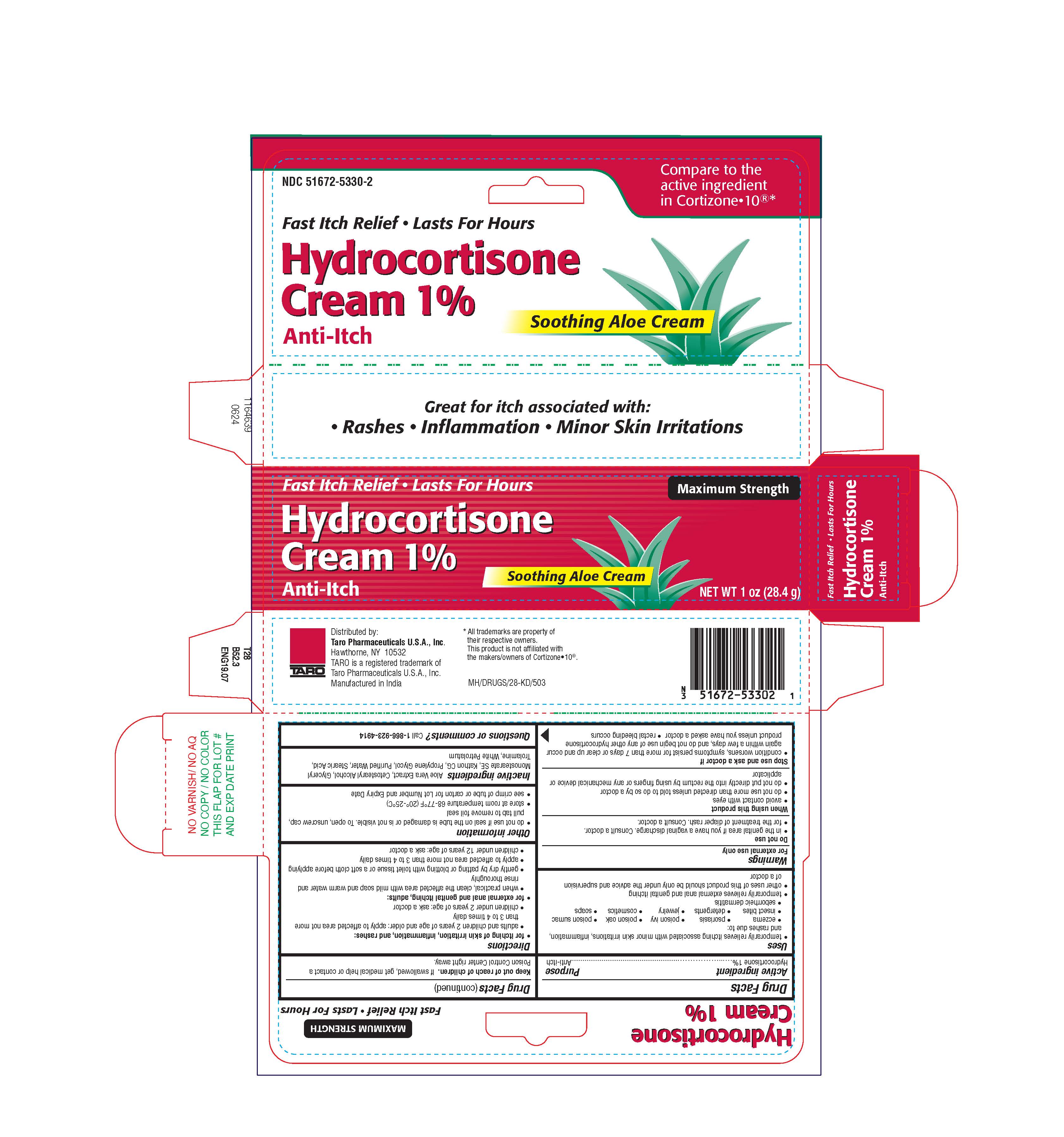 DRUG LABEL: Hydrocortisone

NDC: 51672-5330 | Form: CREAM
Manufacturer: Sun Pharmaceutical Industries, Inc.
Category: otc | Type: HUMAN OTC DRUG LABEL
Date: 20250616

ACTIVE INGREDIENTS: HYDROCORTISONE 1 g/100 g
INACTIVE INGREDIENTS: STEARYL ALCOHOL; WHITE PETROLATUM; TROLAMINE; STEARIC ACID; ALOE VERA LEAF; CETOSTEARYL ALCOHOL; METHYLCHLOROISOTHIAZOLINONE/METHYLISOTHIAZOLINONE MIXTURE; GLYCERYL MONOSTEARATE; WATER

Hydrocortisone Cream 1% with Aloe

Drug Facts

Active ingredient

Hydrocortisone 1%

Purpose

Anti-itch

Uses

- temporarily relieves of itching associated with minor skin irritations, inflammation, and rashes due to
  - eczema
  - insect bites
  - poison ivy
  - poison oak
  - poison sumac
  - soaps
  - detergents
  - cosmetics
  - jewelry
  - seborrheic dermatitis
  - psoriasis
- temporarily relieves external anal and genital itching
- other uses of this product should be only under the advice and supervision of a doctor

Warnings

For external use only

Do not use

- in the genital area if you have a vaginal discharge. Consult a doctor.
- for the treatment of diaper rash. Consult a doctor.

When using this product

- avoid contact with eyes
- do not use more than directed unless told to do so by a doctor
- do not put directly into the rectum by using fingers or any mechanical device or applicator

Stop use and ask a doctor if

- condition worsens, symptoms persist for more than 7 days or clear up and occur again within a few days, and do not begin use of any other hydrocortisone product unless you have asked a doctor
- rectal bleeding occurs

Keep out of reach of children. If swallowed, get medical help or contact a Poison Control Center right away.

Directions

- for itching of skin irritation, inflammation, and rashes
- adults and children 2 years of age and older: apply to affected area not more than 3 to 4 times daily
- children under 2 years of age: ask a doctor

- for external anal and genital itching, adults:
- when practical, clean the affected area with mild soap and warm water and rinse thoroughly
- gently dry by patting or blotting with toilet tissue or a soft cloth before applying
- apply to affected area not more than 3 to 4 times daily
- children under 12 years of age: ask a doctor

Other information

- do not use if seal on the tube is damaged or is not visible. To open, unscrew cap, pull tab to remove foil seal
- store at room temperature 68-77°F (20°-25°C)
- see crimp of tube or carton for Lot Number and Expiry Date

Inactive ingredients

Aloe Vera Extract, Cetostearyl Alcohol, Glyceryl Monostearate SE, Kathon CG, Propylene Glycol, Purified Water, Stearic Acid, Trolamine, White Petrolatum

Questions or Comments?

Call 1-866-923-4914

Distributed by:
Ohm Laboratories Inc.
New Brunswick, NJ 08901

Manufactured in India

MH/DRUGS/28-KD/503

PRINCIPAL DISPLAY PANEL - 28.4 g Carton

MAXIMUM STRENGTH

Hydrocortisone Cream 1%

Soothing Aloe Cream

NET WT 1 oz (28.4 g)